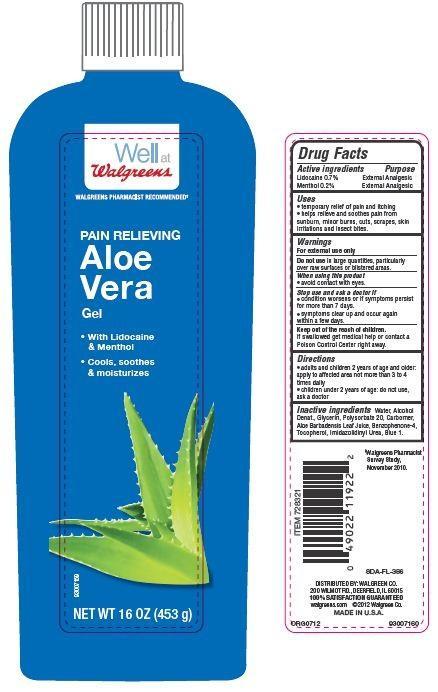 DRUG LABEL: Walgreens
NDC: 0363-4012 | Form: GEL
Manufacturer: WALGREEN CO.
Category: otc | Type: HUMAN OTC DRUG LABEL
Date: 20130807

ACTIVE INGREDIENTS: LIDOCAINE 0.7 g/100 g; MENTHOL 0.2 g/100 g
INACTIVE INGREDIENTS: WATER; SULISOBENZONE; TOCOPHEROL; ALOE VERA LEAF; GLYCERIN; POLYSORBATE 20; IMIDUREA

Drug Facts

Active ingredients

Lidocaine 0.7%

Menthol 0.2%

Purpose

External Analgesic

External Analgesic

Uses

- temporary relief of pain and itching
- helps relieve and soothes pain from sunburn, minor burns, cuts, scrapes, skin irritations and insect bites.

Warnings

For external use only

Do not use in large quantities, particularly over raw surfaces or blistered areas.

When using this product

- avoid contact with eyes.

Stop use and ask a doctor if

- conditions worsens or if symptoms persists for more than 7 days.
- symptoms clear up and occur again within a few days.

Keep out of the reach of children.

If swallowed get medical help or contact a Poison Control Center right away.

Directions

- adults and children 2 years of age and older.apply to affected area not more than 3 to 4 times daily
- children under 2 years of age: do not use, ask a doctor.

Inactive ingredients

Water, Alcohol Denat., Glycerin, Polysorbate 20, Carbomer, Aloe Barbadensis Leaf Juice, Benzophenone-4, Tocopherol, Imidazolidinyl Urea, Blue 1.

Principal Display Panel

Well at

Walgreens

WALGREENS PHARMACIST RECOMMENDED

PAIN RELIEVING

Aloe

Vera

Gel

With Lidocaine

and Menthol

Cools, soothes

and moisturizes

NET WT 16 OZ (453 g)